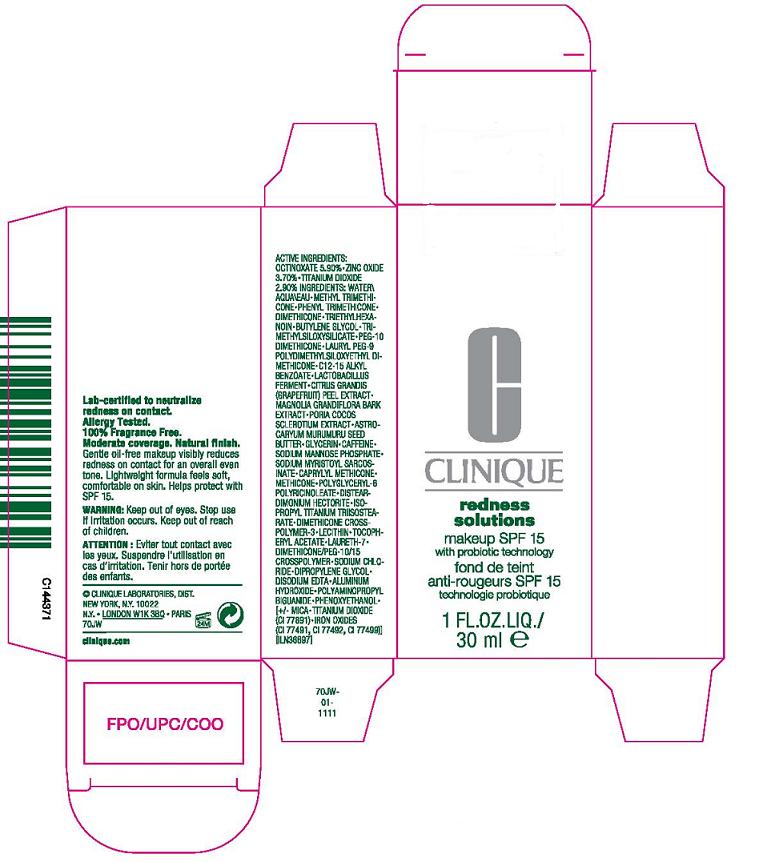 DRUG LABEL: REDNESS SOLUTIONS MAKEUP
NDC: 49527-005 | Form: LOTION
Manufacturer: CLINIQUE LABORATORIES INC
Category: otc | Type: HUMAN OTC DRUG LABEL
Date: 20110707

ACTIVE INGREDIENTS: OCTINOXATE 5.9 mL/100 mL; ZINC OXIDE 3.7 mL/100 mL; TITANIUM DIOXIDE 2.9 mL/100 mL
INACTIVE INGREDIENTS: WATER; METHYL TRIMETHICONE; PHENYL TRIMETHICONE; DIMETHICONE; TRIETHYLHEXANOIN; BUTYLENE GLYCOL; TRIMETHOXYCAPRYLYLSILANE; ALUMINUM HYDROXIDE; ALKYL (C12-15) BENZOATE; LACTOBACILLUS HELVETICUS; CITRUS MAXIMA FRUIT RIND; MAGNOLIA GRANDIFLORA BARK; FU LING; ASTROCARYUM MURUMURU SEED BUTTER; GLYCERIN; CAFFEINE; SODIUM MYRISTOYL ISETHIONATE; LECITHIN, SOYBEAN; ALPHA-TOCOPHEROL ACETATE; LAURETH-7; SODIUM CHLORIDE; DIPROPYLENE GLYCOL; EDETATE DISODIUM; POLYAMINOPROPYL BIGUANIDE; PHENOXYETHANOL; MICA; FERRIC OXIDE RED

ACTIVE INGREDIENT

active ingredients: octinoxate 5.90% [] titanium dioxide 3.70% [] zinc oxide 2.90%

INACTIVE INGREDIENT

inactive ingredients: water [] methyl trimethicone [] phenyl trimethicone [] dimethicone [] triethylhexanoin [] butylene glycol [] trimethylsiloxysilicate [] peg-10 dimethicone [] lauryl peg-9 polydimethylsiloxyethyl dimethicone [] aluminum hydroxide [] c12-15 alkyl benzoate [] lactobacillus ferment [] citrus grandis (grapefruit) peel extract [] magnolia grandiflora bark extract [] poria cocos sclerotium extract [] astrocaryum murumuru seed butter [] glycerin [] caffeine [] sodium myristoyl sarcosinate [] caprylyl methicone [] methicone [] polyglyceryl-6 polyricinoleate [] disteardimonium hectorite [] acetyl glucosamine [] isopropyl titanium triisostearate [] dimethicone crosspolymer-3 [] lecithin [] tocopheryl acetate [] laureth-7 [] dimethicone/peg-10/15 crosspolymer [] sodium chloride [] dipropylene glycol [] disodium edta [] polyaminopropyl biguanide [] phenoxyethanol [] [+/- mica [] titanium dioxide (ci 77891) [] iron oxides (ci 77491, ci 77492, ci 77499)]

WARNINGS

warning: keep out of eyes. discontinue use if irritation occurs. keep out of reach of children.

PACKAGE LABEL

principal display panel:

CLINIQUE

REDNESS

SOLUTIONS

MAKE UP SPF 15

with probiotic technology

1 fl oz liq/ 30 ml

clinique laboratories, dist

new york, ny 10022